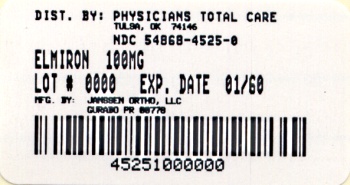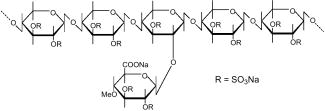 DRUG LABEL: Elmiron
NDC: 54868-4525 | Form: CAPSULE, GELATIN COATED
Manufacturer: Physicians Total Care, Inc.
Category: prescription | Type: HUMAN PRESCRIPTION DRUG LABEL
Date: 20100308

ACTIVE INGREDIENTS: PENTOSAN POLYSULFATE SODIUM 100 mg/1 1
INACTIVE INGREDIENTS: CELLULOSE, MICROCRYSTALLINE; MAGNESIUM STEARATE; FERROSOFERRIC OXIDE; FD&C BLUE NO. 2; FD&C RED NO. 40; FD&C BLUE NO. 1; D&C YELLOW NO. 10; ALUMINUM OXIDE; BUTYL ALCOHOL; PROPYLENE GLYCOL; TITANIUM DIOXIDE

ELMIRON®-100 mg
(pentosan polysulfate sodium)
Capsules

PRESCRIBING INFORMATION

DESCRIPTION

Pentosan polysulfate sodium is a semi-synthetically produced heparin-like macromolecular carbohydrate derivative, which chemically and structurally resembles glycosaminoglycans. It is a white odorless powder, slightly hygroscopic and soluble in water to 50% at pH 6. It has a molecular weight of 4000 to 6000 Dalton with the following structural formula:

ELMIRON® is supplied in white opaque hard gelatin capsules containing 100 mg pentosan polysulfate sodium, microcrystalline cellulose, and magnesium stearate. It also contains pharmaceutical glaze (modified) in SD-45, synthetic black iron oxide, FD&C Blue No. 2 aluminum lake, FD&C Red No. 40 aluminum lake, FD&C Blue No. 1 aluminum lake, D&C Yellow No. 10 aluminum lake, n-butyl alcohol, propylene glycol, SDA-3A alcohol, and titanium dioxide. It is formulated for oral use.

CLINICAL PHARMACOLOGY

General

Pentosan polysulfate sodium is a low molecular weight heparin-like compound. It has anticoagulant and fibrinolytic effects. The mechanism of action of pentosan polysulfate sodium in interstitial cystitis is not known.

Pharmacokinetics

Absorption

In a clinical pharmacology study in which healthy female volunteers received a single oral 300 or 450 mg dose of pentosan polysulfate sodium containing radiolabeled drug as a solution under fasted conditions, maximal levels of plasma radioactivity were seen approximately at a median of 2 hours (range 0.6–120 hours) after dosing. Based on urinary excretion of radioactivity, a mean of approximately 6% of a radiolabeled oral dose of pentosan polysulfate sodium is absorbed and reaches the systemic circulation.

Food Effects

In clinical trials, ELMIRON® was administered with water 1 hour before or 2 hours after meals; the effect of food on absorption of pentosan polysulfate sodium is not known.

Distribution

Preclinical studies with parenterally administered radiolabeled pentosan polysulfate sodium showed distribution to the uroepithelium of the genitourinary tract with lesser amounts found in the liver, spleen, lung, skin, periosteum, and bone marrow. Erythrocyte penetration is low in animals.

Metabolism

The fraction of pentosan polysulfate sodium that is absorbed is metabolized by partial desulfation in the liver and spleen, and by partial depolymerization in the kidney to a large number of metabolites. Both the desulfation and depolymerization can be saturated with continued dosing.

Excretion

Following administration of an oral solution of a 300 or 450 mg dose of pentosan polysulfate sodium containing radiolabeled drug to groups of healthy subjects, plasma radioactivity declined with mean half-lives of 27 and 20 hours, respectively. A large proportion of the orally administered dose of pentosan polysulfate sodium (mean 84% in the 300 mg group and 58% in the 450 mg group) is excreted in feces as unchanged drug. A mean of 6% of an oral dose is excreted in the urine, mostly as desulfated and depolymerized metabolites. Only a small fraction of the administered dose (mean 0.14%) is recovered as intact drug in urine.

Special Populations

The pharmacokinetics of pentosan polysulfate sodium has not been studied in geriatric patients or in patients with hepatic or renal impairment. See also PRECAUTIONS-Hepatic Insufficiency.

Drug-Drug Interactions

In a study in which healthy subjects received pentosan polysulfate sodium 100 mg capsule or placebo every 8 hours for 7 days, and were titrated with warfarin to an INR of 1.4 to 1.8, the pharmacokinetic parameters of R-warfarin and S-warfarin were similar in the absence and presence of pentosan polysulfate sodium. INR for warfarin + placebo and warfarin + pentosan polysulfate sodium were comparable. See also PRECAUTIONS on the use of ELMIRON® in patients receiving other therapies with anticoagulant effects.

Pharmacodynamics

The mechanism by which pentosan polysulfate sodium achieves its effects in patients is unknown. In preliminary clinical models, pentosan polysulfate sodium adhered to the bladder wall mucosal membrane. The drug may act as a buffer to control cell permeability preventing irritating solutes in the urine from reaching the cells.

CLINICAL TRIALS

ELMIRON® was evaluated in two clinical trials for the relief of pain in patients with chronic interstitial cystitis (IC). All patients met the NIH definition of IC based upon the results of cystoscopy, cytology, and biopsy. One blinded, randomized, placebo controlled study evaluated 151 patients (145 women, 5 men, 1 unknown) with a mean age of 44 years (range 18 to 81). Approximately equal numbers of patients received either placebo or ELMIRON® 100 mg three times a day for 3 months. Clinical improvement in bladder pain was based upon the patient's own assessment. In this study, 28/74 (38%) of patients who received ELMIRON® and 13/74 (18%) of patients who received placebo, showed greater than 50% improvement in bladder pain (p=0.005).

A second clinical trial, the physician's usage study, was a prospectively designed retrospective analysis of 2499 patients who received ELMIRON® 300 mg a day without blinding. Of the 2499 patients, 2220 were women, 254 were men, and 25 were of unknown sex. The patients had a mean age of 47 years and 23% were over 60 years of age. By 3 months, 1307 (52%) of the patients had dropped out or were ineligible for analysis, overall, 1192 (48%) received ELMIRON® for 3 months; 892 (36%) received ELMIRON® for 6 months; and 598 (24%) received ELMIRON® for one year.

Patients had unblinded evaluations every 3 months for the patient's rating of overall change in pain in comparison to baseline and for the difference calculated in "pain/discomfort" scores. At baseline, pain/discomfort scores for the original 2499 patients were severe or unbearable in 60%, moderate in 33% and mild or none in 7% of patients. The extent of the patients' pain improvement is shown in Table 1.

At 3 months, 722/2499 (29%) of the patients originally in the study had pain scores that improved by one or two categories. By 6 months, in the 892 patients who continued taking ELMIRON®, an additional 116/2499 (5%) of patients had improved pain scores. After 6 months, the percent of patients who reported the first onset of pain relief was less than 1.5% of patients who originally entered in the study (see Table 2).

Table 1: Pain Scores in Reference to Baseline in Open Label Physician's Usage Study (N=2499) [Trial not designed to detect onset of pain relief]
Efficacy Parameter | 3 months [CI = 95% confidence interval] | 6 months
Patient Rating of Overall Change in Pain (Recollection of difference between current pain and baseline pain) [6-point scale: 1 = worse, 2 = no better, 3 = slightly improved, 4 = moderately improved, 5 = greatly improved, 6 = symptom gone] | N=1161 Median=3 Mean=3.44 CI: (3.37, 3.51) | N=724 Median=4 Mean=3.91 CI: (3.83, 3.99)
Change in Pain/Discomfort Score (Calculated difference in scores at the time point and baseline) [3-point scale: 1 = none or mild, 2 = moderate, 3 = severe or unbearable] | N=1440 Median=1 Mean=0.51 CI: (0.45, 0.57) | N=904 Median=1 Mean=0.66 CI: (0.61, 0.71)

Table 2: Number (%) of Patients with New Relief of Pain/Discomfort [First-time Improvement in pain/discomfort score by 1 or 2 categories] in the Open-Label Physician's Usage Study (N=2499)
 | at 3 months [Number (%) of patients with improvement of pain/discomfort score at 3 months when compared to baseline] (n=1192) | at 6 months [Number (%) of patients without pain/discomfort improvement at 3 months who had improvement at 6 months] (n=892)
Considering only the patients who continued treatment | 722/1192 (61%) | 116/892 (13%)
Considering all the patients originally enrolled in the study | 722/2499 (29%) | 116/2499 (5%)

INDICATIONS AND USAGE

ELMIRON® (pentosan polysulfate sodium) is indicated for the relief of bladder pain or discomfort associated with interstitial cystitis.

CONTRAINDICATIONS

ELMIRON® is contraindicated in patients with known hypersensitivity to the drug, structurally related compounds, or excipients.

WARNINGS

None.

PRECAUTIONS

General

ELMIRON® is a weak anticoagulant (1/15 the activity of heparin). At a daily dose of 300 mg (n = 128), rectal hemorrhage was reported as an adverse event in 6.3% of patients. Bleeding complications of ecchymosis, epistaxis, and gum hemorrhage have been reported (see ADVERSE REACTIONS). Patients undergoing invasive procedures or having signs/symptoms of underlying coagulopathy or other increased risk of bleeding (due to other therapies such as coumarin anticoagulants, heparin, t-PA, streptokinase, high dose aspirin, or nonsteroidal anti-inflammatory drugs) should be evaluated for hemorrhage. Patients with diseases such as aneurysms, thrombocytopenia, hemophilia, gastrointestinal ulcerations, polyps, or diverticula should be carefully evaluated before starting ELMIRON®.

A similar product that was given subcutaneously, sublingually, or intramuscularly (and not initially metabolized by the liver) is associated with delayed immunoallergic thrombocytopenia with symptoms of thrombosis and hemorrhage. Caution should be exercised when using ELMIRON® in patients who have a history of heparin induced thrombocytopenia.

Alopecia is associated with pentosan polysulfate and with heparin products. In clinical trials of ELMIRON®, alopecia began within the first 4 weeks of treatment. Ninety-seven percent (97%) of the cases of alopecia reported were alopecia areata, limited to a single area on the scalp.

Hepatic Insufficiency

ELMIRON® has not been studied in patients with hepatic insufficiency. Because there is evidence of hepatic contribution to the elimination of ELMIRON®, hepatic impairment may have an impact on the pharmacokinetics of ELMIRON®. Caution should be exercised when using ELMIRON® in this patient population.

Mildly (<2.5 × normal) elevated transaminase, alkaline phosphatase, γ-glutamyl transpeptidase, and lactic dehydrogenase occurred in 1.2% of patients. The increases usually appeared 3 to 12 months after the start of ELMIRON® therapy, and were not associated with jaundice or other clinical signs or symptoms. These abnormalities are usually transient, may remain essentially unchanged, or may rarely progress with continued use. Increases in PTT and PT (<1% for both) or thrombocytopenia (0.2%) were noted.

Information for Patients

Patients should take the drug as prescribed, in the dosage prescribed, and no more frequently than prescribed. Patients should be reminded that ELMIRON® has a weak anticoagulant effect. This effect may increase bleeding times.

Laboratory Test Findings

Pentosan polysulfate sodium did not affect prothrombin time (PT) or partial thromboplastin time (PTT) up to 1200 mg per day in 24 healthy male subjects treated for 8 days. Pentosan polysulfate sodium also inhibits the generation of factor Xa in plasma and inhibits thrombin-induced platelet aggregation in human platelet rich plasma ex vivo. (See PRECAUTIONS-Hepatic Insufficiency Section for additional information.)

Carcinogenicity, Mutagenesis, Impairment of Fertility

Long term carcinogenicity studies of ELMIRON® in F344/N rats and B6C3F1 mice have been conducted. In these studies, ELMIRON® was orally administered once daily via gavage, 5 days per week, for up to 2 years. The dosages administered to mice were 56, 168 or 504 mg/kg. The dosages administered to rats were 14, 42, or 126 mg/kg for males, and 28, 84, or 252 mg/kg for females. The dosages tested were up to 60 times the maximum recommended human dose (MRHD) in rats, and up to 117 times the MRHD in mice, on a mg/kg basis. The results of these studies in rodents showed no clear evidence of drug-related tumorigenesis or carcinogenic risk.

Pentosan polysulfate sodium was not clastogenic or mutagenic when tested in the mouse micronucleus test or the Ames test (S. typhimurium). The effect of pentosan polysulfate sodium on spermatogenesis has not been investigated.

Pregnancy Category B

TERATOGENIC EFFECTS

Reproduction studies have been performed in mice and rats with intravenous daily doses of 15 mg/kg, and in rabbits with 7.5 mg/kg. These doses are 0.42 and 0.14 times the daily oral human doses of ELMIRON® when normalized to body surface area. These studies did not reveal evidence of impaired fertility or harm to the fetus from ELMIRON®. Direct in vitro bathing of cultured mouse embryos with pentosan polysulfate sodium (PPS) at a concentration of 1 mg/mL may cause reversible limb bud abnormalities. Adequate and well-controlled studies have not been performed in pregnant women. Because animal studies are not always predictive of human response, this drug should be used in pregnancy only if clearly needed.

Nursing Mothers

It is not known whether this drug is excreted in human milk. Because many drugs are excreted in human milk, caution should be exercised when ELMIRON® is administered to a nursing woman.

Pediatric Use

Safety and effectiveness in pediatric patients below the age of 16 years have not been established.

ADVERSE REACTIONS

ELMIRON® was evaluated in clinical trials in a total of 2627 patients (2343 women, 262 men, 22 unknown) with a mean age of 47 [range 18 to 88 with 581 (22%) over 60 years of age]. Of the 2627 patients, 128 patients were in a 3 month trial and the remaining 2499 patients were in a long term, unblinded trial.

Deaths occurred in 6/2627 (0.2%) patients who received the drug over a period of 3 to 75 months. The deaths appear to be related to other concurrent illnesses or procedures, except in one patient for whom the cause was not known.

Serious adverse events occurred in 33/2627 (1.3%) patients. Two patients had severe abdominal pain or diarrhea and dehydration that required hospitalization. Because there was not a control group of patients with interstitial cystitis who were concurrently evaluated, it is difficult to determine which events are associated with ELMIRON® and which events are associated with concurrent illness, medicine, or other factors.

Adverse Experience In Placebo-Controlled Clinical Trials of ELMIRON® 100 mg Three Times a Day for 3 Months
Body System/Adverse Experience | ELMIRON® n=128 | Placebo n=130
CNS Overall Number of Patients [Within a body system, the individual events do not sum to equal overall number of patients because a patient may have more than one event.] | 3 | 5
Insomnia | 1 | 0
Headache | 1 | 3
Severe Emotional Lability/Depression | 2 | 1
Nystagmus/Dizziness | 1 | 1
Hyperkinesia | 1 | 1
GI Overall Number of Patients | 7 | 7
Nausea | 3 | 3
Diarrhea | 3 | 6
Dyspepsia | 1 | 0
Jaundice | 0 | 1
Vomiting | 0 | 2
Skin/Allergic Overall Number of Patients | 2 | 4
Rash | 0 | 2
Pruritus | 0 | 2
Lacrimation | 1 | 1
Rhinitis | 1 | 1
Increased Sweating | 1 | 0
Other Overall Number of Patients | 1 | 3
Amenorrhea | 0 | 1
Arthralgia | 0 | 1
Vaginitis | 1 | 1
Total Events | 17 | 27
Total Number of Patients
Reporting Adverse Events | 13 | 19

The adverse events described below were reported in an unblinded clinical trial of 2499 interstitial cystitis patients treated with ELMIRON®. Of the original 2499 patients, 1192 (48%) received ELMIRON® for 3 months; 892 (36%) received ELMIRON for 6 months; and 598 (24%) received ELMIRON® for one year, 355 (14%) received ELMIRON® for 2 years, and 145 (6%) for 4 years.

Frequency (1 to 4%): Alopecia (4%), diarrhea (4%), nausea (4%), headache (3%), rash (3%), dyspepsia (2%), abdominal pain (2%), liver function abnormalities (1%), dizziness (1%).

Frequency (≤ 1%):

Digestive: Vomiting, mouth ulcer, colitis, esophagitis, gastritis, flatulence, constipation, anorexia, gum hemorrhage.

Hematologic: Anemia, ecchymosis, increased prothrombin time, increased partial thromboplastin time, leukopenia, thrombocytopenia.

Hypersensitive Reactions: Allergic reaction, photosensitivity.

Respiratory System: Pharyngitis, rhinitis, epistaxis, dyspnea.

Skin and Appendages: Pruritus, urticaria.

Special Senses: Conjunctivitis, tinnitus, optic neuritis, amblyopia, retinal hemorrhage.

Post-Marketing Experience

Rectal Hemorrhage

ELMIRON® was evaluated in a randomized, double-blind, parallel group, Phase 4 study conducted in 380 patients with interstitial cystitis dosed for 32 weeks. At a daily dose of 300 mg (n = 128), rectal hemorrhage was reported as an adverse event in 6.3% of patients. The severity of the events was described as "mild" in most patients. Patients in that study who were administered ELMIRON® 900 mg daily, a dose higher than the approved dose, experienced a higher incidence of rectal hemorrhage, 15%.

Liver Function Abnormality

A randomized, double-blind, parallel group, phase 2 study was conducted in 100 men (51 ELMIRON® and 49 placebo) dosed for 16 weeks. At a daily dose of 900 mg, a dose higher than the approved dose, elevated liver function tests were reported as an adverse event in 11.8% (n = 6) of ELMIRON® treated patients and 2% (n = 1) of placebo treated patients.

OVERDOSAGE

Overdose has not been reported. Based upon the pharmacodynamics of the drug, toxicity is likely to be reflected as anticoagulation, bleeding, thrombocytopenia, liver function abnormalities, and gastric distress. (See CLINICAL PHARMACOLOGY and PRECAUTIONS sections.) At a daily dose of 900 mg for 32 weeks (n = 127) in a clinical trial, rectal hemorrhage was reported as an adverse event in 15% of patients. At a daily dose of ELMIRON® 900 mg for 16 weeks in a clinical trial that enrolled 51 patients in the ELMIRON® group and 49 in the placebo group, elevated liver function tests were reported as an adverse event in 11.8% of patients in the ELMIRON® group and 2% of patients in the placebo group. In the event of acute overdosage, the patient should be given gastric lavage if possible, carefully observed and given symptomatic and supportive treatment.

DOSAGE AND ADMINISTRATION

The recommended dose of ELMIRON® is 300 mg/day taken as one 100 mg capsule orally three times daily. The capsules should be taken with water at least 1 hour before meals or 2 hours after meals.

Patients receiving ELMIRON® should be reassessed after 3 months. If improvement has not occurred and if limiting adverse events are not present, ELMIRON® may be continued for another 3 months.

The clinical value and risks of continued treatment in patients whose pain has not improved by 6 months is not known.

HOW SUPPLIED

ELMIRON® is supplied in white opaque hard gelatin capsules imprinted "BNP7600" containing 100 mg pentosan polysulfate sodium. Supplied in:

NDC 54868-4525-2 | Bottles of 10 capsules
NDC 54868-4525-1 | Bottles of 30 capsules
NDC 54868-4525-3 | Bottles of 90 capsules
NDC 54868-4525-0 | Bottles of 100 capsules

Storage

Store at controlled room temperature 15°–30°C (59°–86°F).

ELMIRON® is a Registered Trademark of Teva Global Respiratory Research, LLC under license to Ortho-McNeil-Janssen Pharmaceuticals, Inc.

© OMJPI 2002,1998

Ortho Women's Health & Urology, Division of Ortho-McNeil-Janssen Pharmaceuticals, Inc.
Raritan, New Jersey 08869

Manufactured by:
Janssen Ortho LLC
Gurabo, Puerto Rico 00778

Manufactured for:
Ortho Women's Health & Urology, Division of Ortho-McNeil-Janssen Pharmaceuticals, Inc.
Raritan, New Jersey 08869

Revised October 2009

10205900

U.S. Patent #5,180,715

Relabeling and Repackaging by:
Physicians Total Care, Inc.
Tulsa, OK 74146

PHARMACIST: PLEASE DISPENSE ONE PATIENT LEAFLET PER PRESCRIPTION

Patient Leaflet

Questions and Answers About

ELMIRON®
(Generic name = pentosan polysulfate sodium)
Capsules

What is the most important information I should know about ELMIRON®?

ELMIRON® (pronounced EL ma ron) is used to treat the pain or discomfort of interstitial cystitis (IC).

You must take ELMIRON® as prescribed by your doctor in the dosage prescribed but no more frequently than prescribed.

ELMIRON® is a weak anticoagulant (blood thinner) which may increase bleeding.

Call your doctor if you will be undergoing surgery or will begin taking anticoagulant therapy such as warfarin sodium, heparin, high doses of aspirin, or anti-inflammatory drugs such as ibuprofen.

What is ELMIRON®?

ELMIRON® is used to treat the pain or discomfort of interstitial cystitis (IC). It is not known exactly how ELMIRON® works, but it is not a pain medication like aspirin or acetaminophen and therefore must be taken continuously for relief as prescribed.

Who should not take ELMIRON®?

- Patients undergoing surgery should speak with their doctor about when to discontinue ELMIRON® prior to surgery.
- ELMIRON® should be used during pregnancy only if clearly needed.

What does your doctor need to know?

- If you are taking anticoagulant therapy such as warfarin sodium, heparin, high doses of aspirin, or anti-inflammatory drugs such as ibuprofen.
- If you are pregnant.
- If you have any liver problems.

How should I take ELMIRON®?

You should take 1 capsule of ELMIRON® by mouth three times a day, with water at least 1 hour before meals or 2 hours after meals. Each capsule contains 100 mg of ELMIRON®.

What should I avoid while taking ELMIRON®?

Anticoagulant therapy such as warfarin sodium, heparin, high doses of aspirin or anti-inflammatory drugs such as ibuprofen until you speak with your doctor.

What are the most common side effects of ELMIRON®?

The most common side effects are hair loss, diarrhea, nausea, blood in the stool, headache, rash, upset stomach, abnormal liver function tests, dizziness and bruising.

Call your doctor if these side effects persist or are bothersome or if there is blood in your stool.

If you suspect that someone may have taken more than the prescribed dose of this medicine, contact your local poison control center or emergency room immediately. This medication was prescribed for your particular condition. Do not use it for another condition or give the drug to others.

This leaflet provides a summary of information about ELMIRON®. Medicines are sometimes prescribed for uses other than those listed in a Patient Leaflet. If you have any questions or concerns, or want more information about ELMIRON®, contact your doctor or pharmacist. Your pharmacist also has a longer leaflet about ELMIRON® that is written for health professionals that you can ask to read.

ELMIRON® is a Registered Trademark of Teva Global Respiratory Research, LLC under license to Ortho-McNeil-Janssen Pharmaceuticals, Inc.

© OMJPI 2002,1998

Ortho Women's Health & Urology, Division of Ortho-McNeil-Janssen Pharmaceuticals, Inc.
Raritan, New Jersey 08869

Revised October 2009

PRINCIPAL DISPLAY PANEL - 100 mg Bottle Label

ELMIRON®
(pentosan polysulfate sodium)
CAPSULES

Rx only

ELMIRON® is a registered trademark
of IVAX Research, LLC under license to
Ortho-McNeil-Janssen Pharmaceuticals, Inc.

100 mg